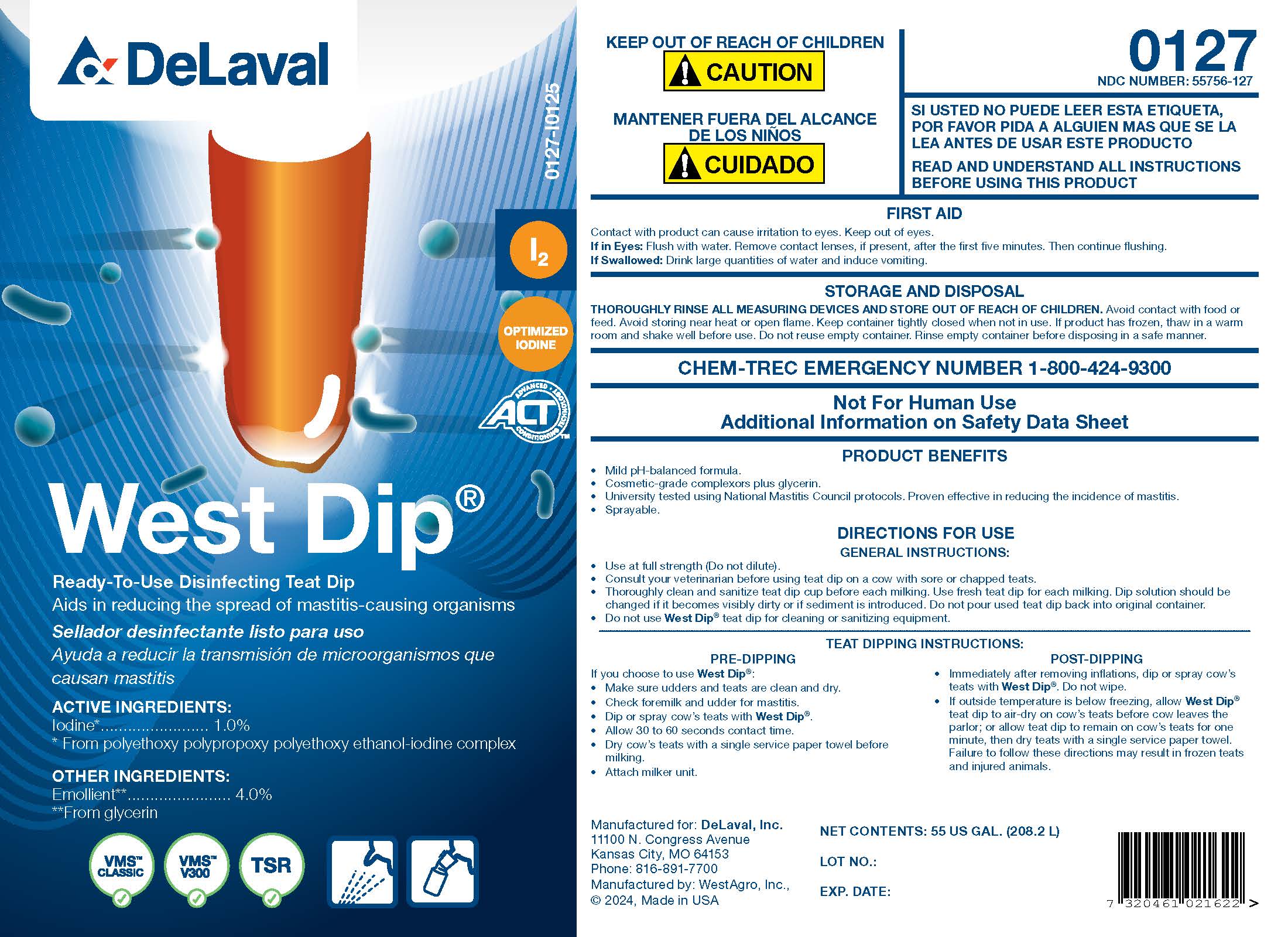 DRUG LABEL: West Dip
NDC: 55756-127 | Form: SOLUTION
Manufacturer: DeLaval, Inc.
Category: animal | Type: OTC ANIMAL DRUG LABEL
Date: 20250304

ACTIVE INGREDIENTS: IODINE 10.2 g/1 L
INACTIVE INGREDIENTS: SODIUM HYDROXIDE; ANHYDROUS CITRIC ACID; GLYCERIN; XANTHAN GUM; SODIUM IODIDE; POLOXAMER 335; DOCUSATE SODIUM; WATER

DeLavalWest Dip®

PURPOSE

Ready-To-Use Disinfecting Teat Dip

Aids in reducing the spread of mastitis-causing organisms

ACTIVE INGREDIENTS:
Iodine* .................................. 1.0%
* From polyethoxy polypropoxy polyethoxy ethanol-iodine complex

OTHER INGREDIENTS:

Emollient** ...................... 4.0%

**From glycerin

KEEP OUT OF REACH OF CHILDREN

! CAUTION

WARNINGS

READ AND UNDERSTAND ALL INSTRUCTIONS BEFORE USING THIS PRODUCT

FIRST AID

Contact with product can cause irritation to eyes. Keep out of eyes.

If in Eyes: Flush with water. Remove contact lenses, if present, after the first five minutes. Then continue flushing.

If Swallowed: Drink large quantities of water and induce vomiting.

STORAGE AND DISPOSAL

THOROUGHLY RINSE ALL MEASURING DEVICES AND STORE OUT OF REACH OF CHILDREN. Avoid contact with food or feed. Avoid storing near heat or open flame. Keep container tightly closed when not in use. If product has frozen, thaw in a warm room and shake well before use. Do not reuse empty container. Rinse empty container before disposing in a safe manner.

CHEM-TREC EMERGENCY NUMBER 1-800-424-9300

WARNINGS AND PRECAUTIONS

Not For Human Use

Additional Information on Safety Data Sheet

PRODUCT BENEFITS

- Mild pH-balanced formula.
- Cosmetic-grade complexors plus glycerin.
- University tested using National Mastitis Council protocols. Proven effective in reducing the incidence of mastitis.
- Sprayable.

DIRECTIONS FOR USE

GENERAL INSTRUCTIONS:

- Use at full strength (Do not dilute).
- Consult your veterinarian before using teat dip on a cow with sore or chapped teats.
- Thoroughly clean and sanitize teat dip cup before each milking. Use fresh teat dip for each milking. Dip solution should be changed if it becomes visibly dirty or if sediment is introduced. Do not pour used teat dip back into original container.
- Do not use West Dip® teat dip for cleaning or sanitizing equipment.

TEAT DIPPING INSTRUCTIONS:

PRE-DIPPING

If you choose to use West Dip®:

- Make sure udders and teats are clean and dry.
- Check foremilk and udder for mastitis.
- Dip or spray cow's teats with West Dip®.
- Allow 30 to 60 seconds contact time.
- Dry cow's teats with a single service paper towel before milking.
- Attach milker unit.

POST-DIPPING

- Immediately after removing inflations, dip or spray cow's teats with West Dip®. Do not wipe.
- If outside temperature is below freezing, allow West Dip® teat dip to air-dry on cow's teats before cow leaves the parlor; or allow teat dip to remain on cow's teats for one minute, then dry teats with a single service paper towel. Failure to follow these directions may result in frozen teats and injured animals.

NET CONTENTS: US Gal. (L)

LOT NO.:

EXP. DATE:

Manufactured for DeLaval, Inc.

11100 N. Congress Avenue

Kansas City, MO 64153

Phone: 816-891-7700

Manufactured by: WestAgro, Inc.,

© 2024, Made in USA

PACKAGE LABEL

Add image transcription here...